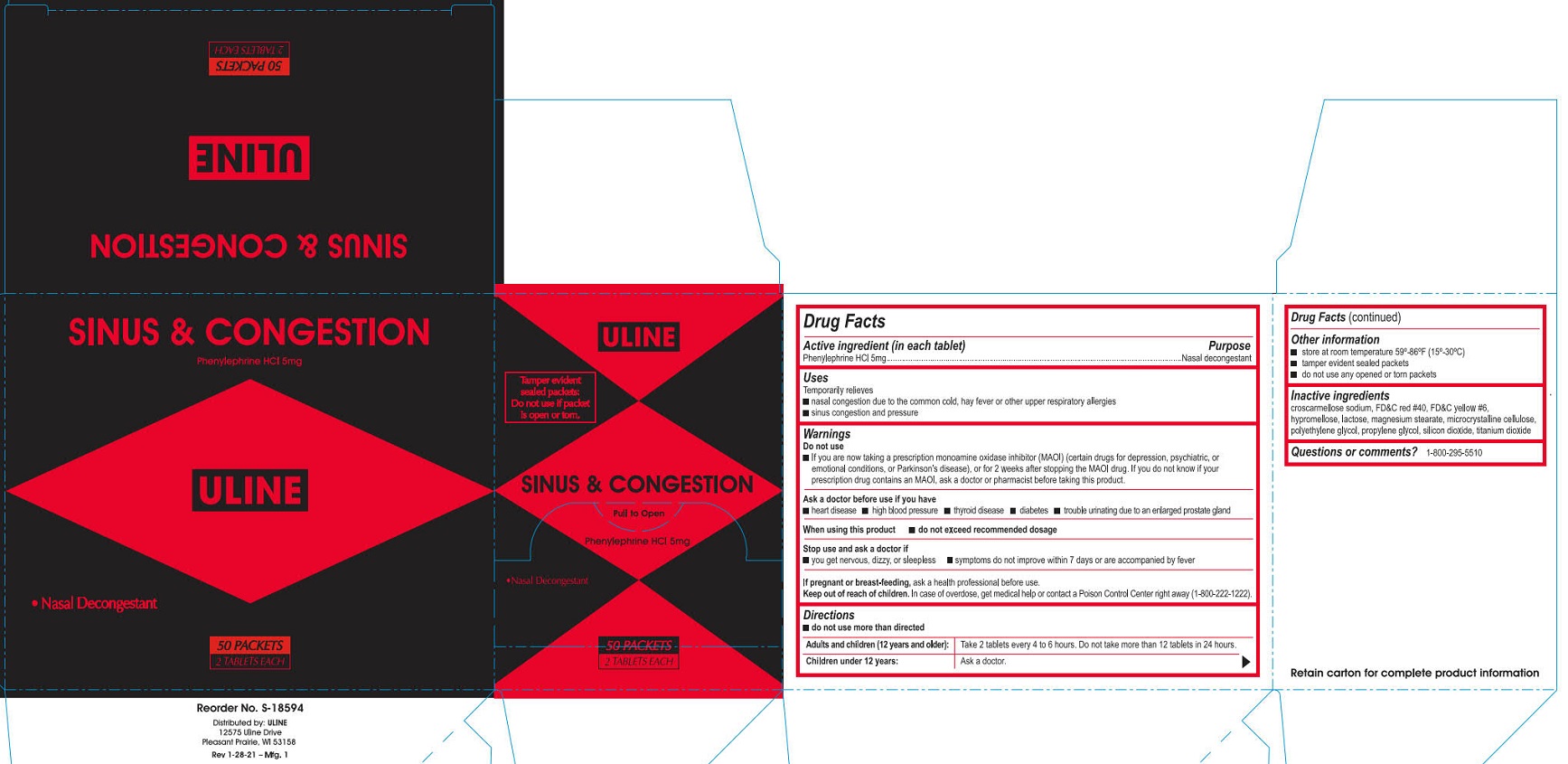 DRUG LABEL: Uline Sinus and Congestion
NDC: 69790-161 | Form: TABLET, FILM COATED
Manufacturer: Uline
Category: otc | Type: HUMAN OTC DRUG LABEL
Date: 20241113

ACTIVE INGREDIENTS: PHENYLEPHRINE HYDROCHLORIDE 5 mg/1 1
INACTIVE INGREDIENTS: PROPYLENE GLYCOL; FD&C RED NO. 40; HYPROMELLOSES; SILICON DIOXIDE; POLYETHYLENE GLYCOL, UNSPECIFIED; TITANIUM DIOXIDE; CELLULOSE, MICROCRYSTALLINE; LACTOSE, UNSPECIFIED FORM; MAGNESIUM STEARATE; FD&C YELLOW NO. 6; CROSCARMELLOSE SODIUM

Uline Sinus & Congestion

Drug Facts

Active ingredient (in each tablet)

Phenylephrine HCl 5mg

Purpose

Nasal decongestant

Uses

Temporarily relieves

- nasal congestion due to the common cold, hay fever or other upper respiratory allergies
- sinus congestion and pressure

Warnings

Do not use

- If you are now taking a prescription monoamine oxidase inhibitor (MAOI) (certain drugs for depression, psychiatric, or emotional conditions, or Parkinson's disease), or for 2 weeks after stopping the MAOI drug. If you do not know if your prescription drug contains an MAOI, ask a doctor or pharmacist before taking this product.

Ask a doctor before use if you have

- heart disease
- high blood pressure
- thyroid disease
- diabetes
- trouble urinating due to an enlarged prostate gland

When using this product

- do not exceed recommended dosage

Stop use and ask a doctor if

- you get nervous, dizzy, or sleepless
- symptoms do not improve within 7 days or are accompanied by fever

PREGNANCY OR BREAST FEEDING

If pregnant or breast-feeding, ask a health professional before use.

Keep out of reach of children.

In case of overdose, get medical help or contact a Poison Control Center right away (1-800-222-1222).

Directions

- do not use more than directed

Adults and children: (12 years and older)

Take 2 tablets every 4 to 6 hours. Do not take more than 12 tablets in 24 hours.

Children under 12 years:

Ask a doctor

Other information

- store at room temperature 59º-86º F (15º-30º C).
- tamper evident sealed packets.
- do not use any opened or torn packets

Inactive ingredients

croscarmellose sodium, FD&C red #40, FD&C yellow #6, hypromellose, lactose, magnesium stearate, microcrystalline cellulose, polyethylene glycol, propylene glycol, silicon dioxide, titanium dioxide

Questions or comments? 1-800-295-5510

PACKAGE LABEL

ULINE

Sinus & Congestion

Phenylephrine HCl 5mg

•Nasal Decongestant

Tamper evident sealed packets:

Do not use if packet is open or torn.

Pull to Open

50 Packets

2 tablets Each